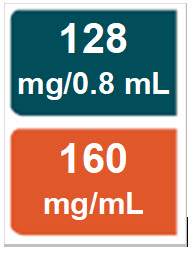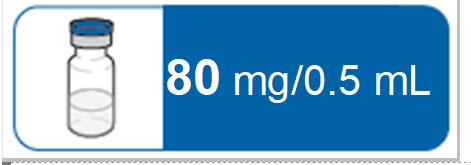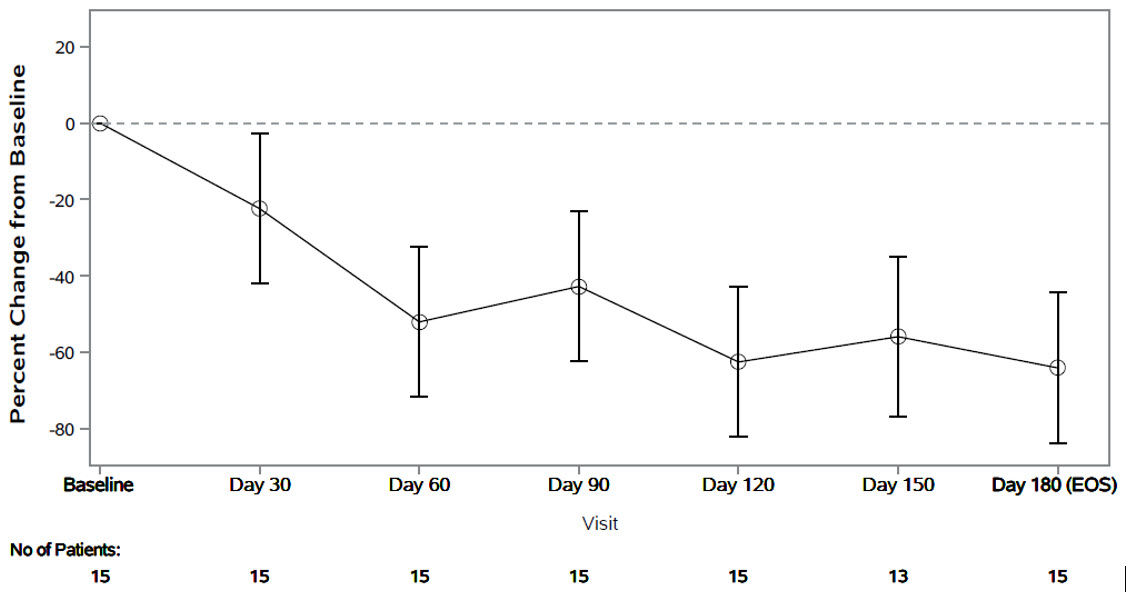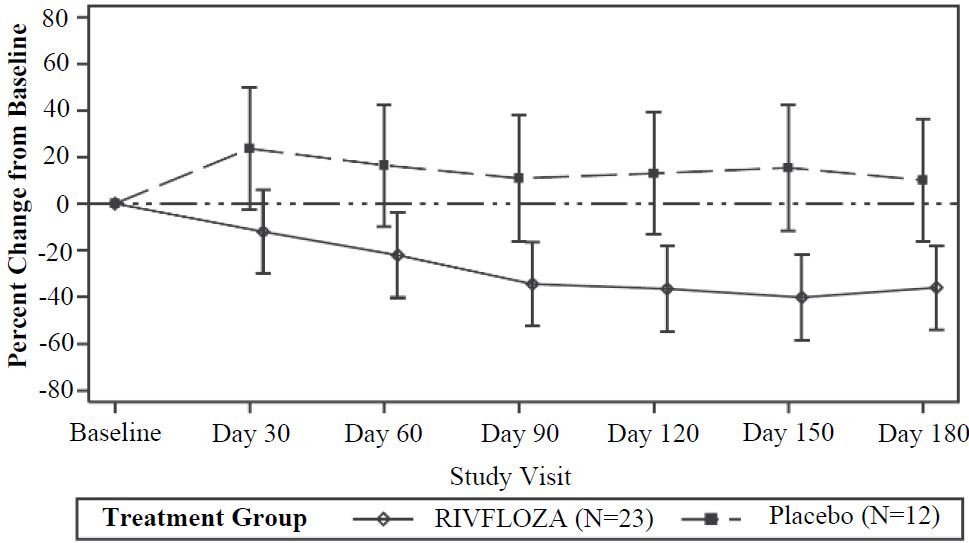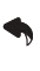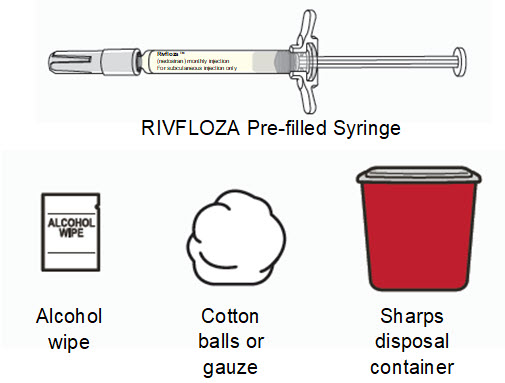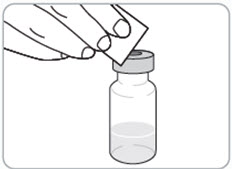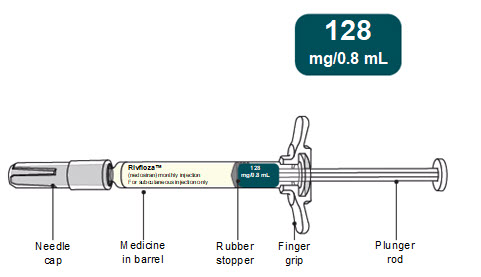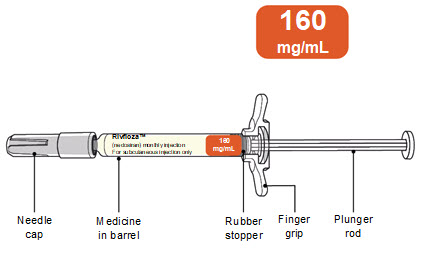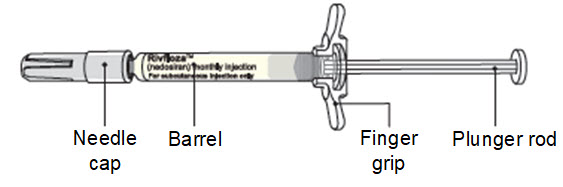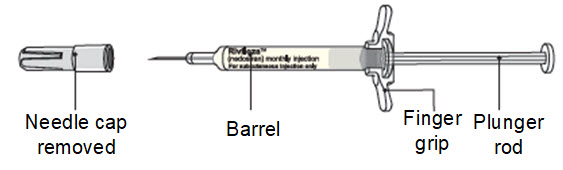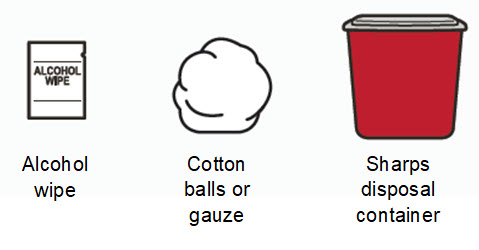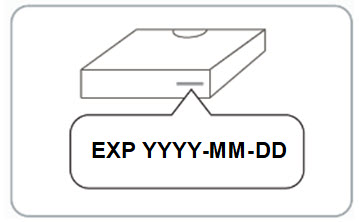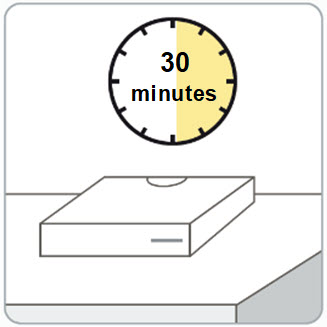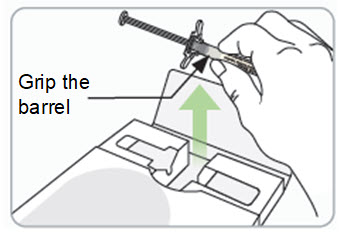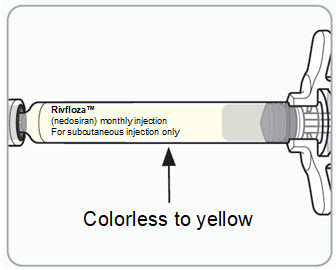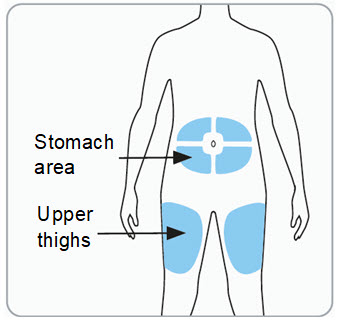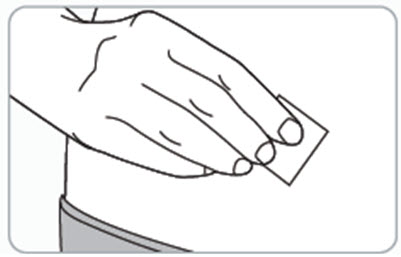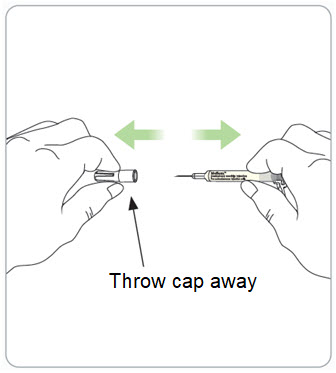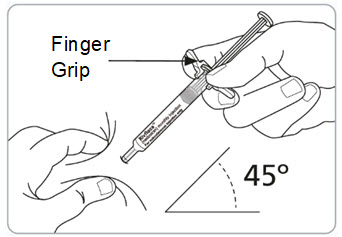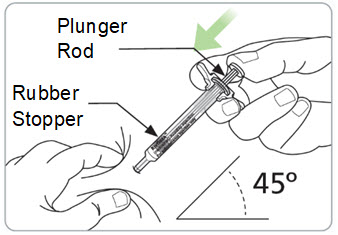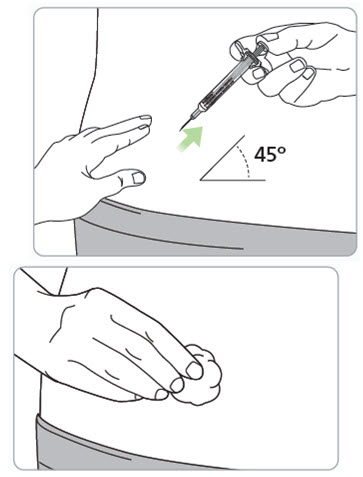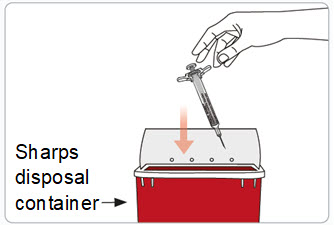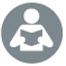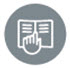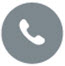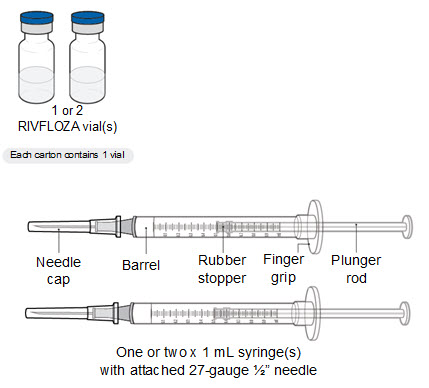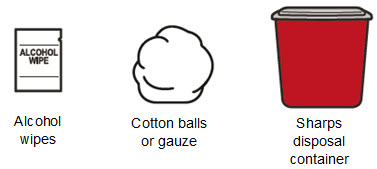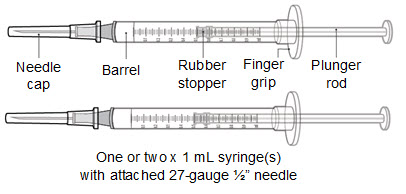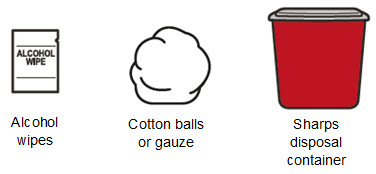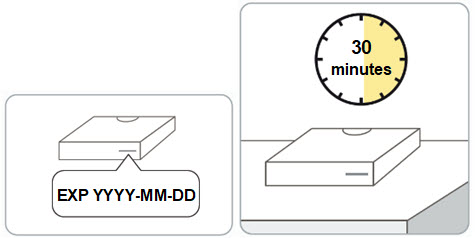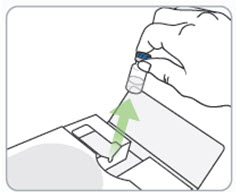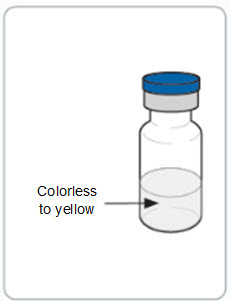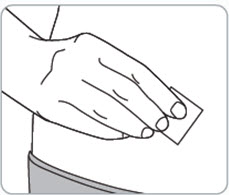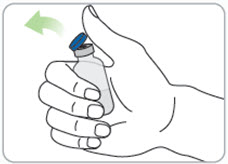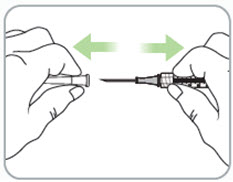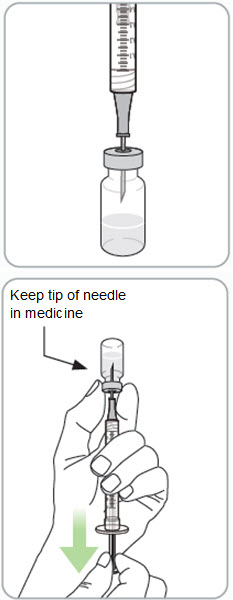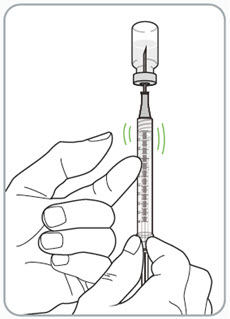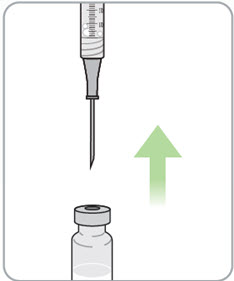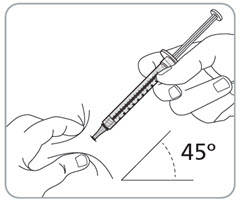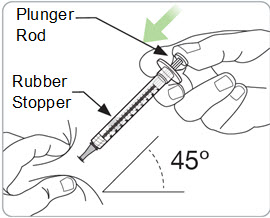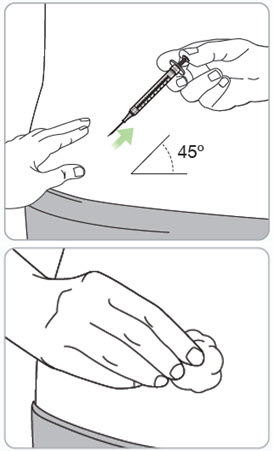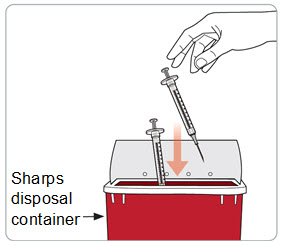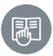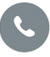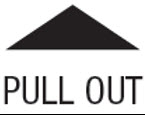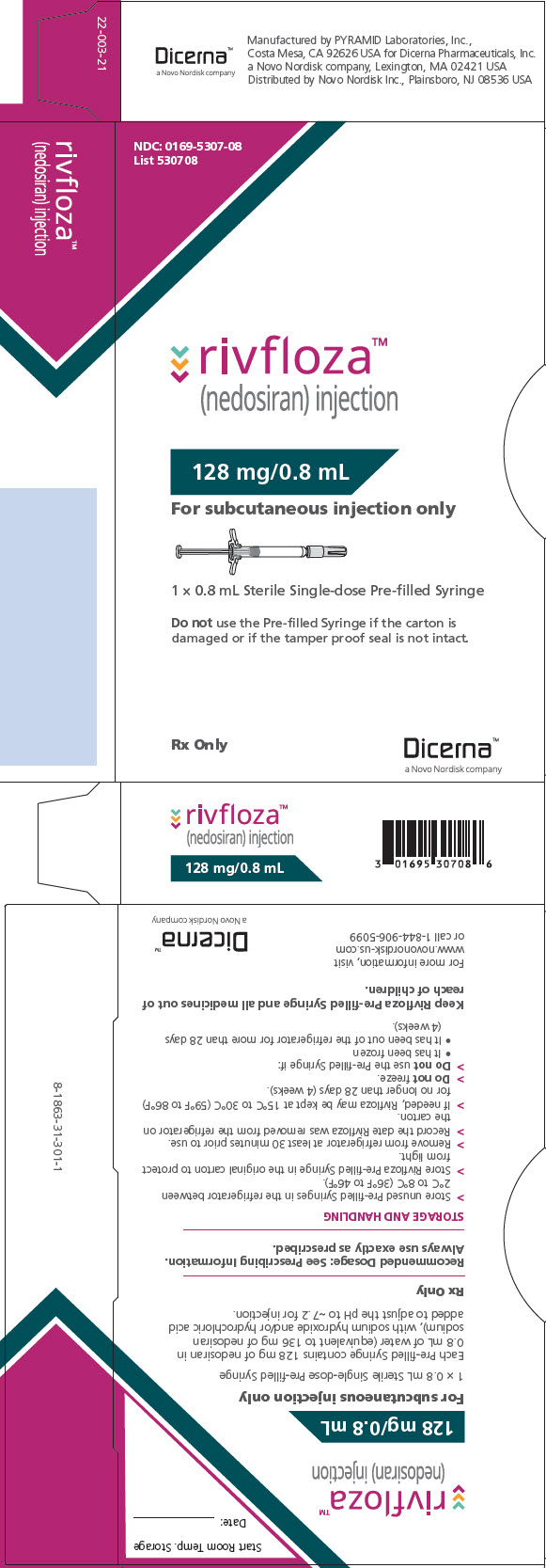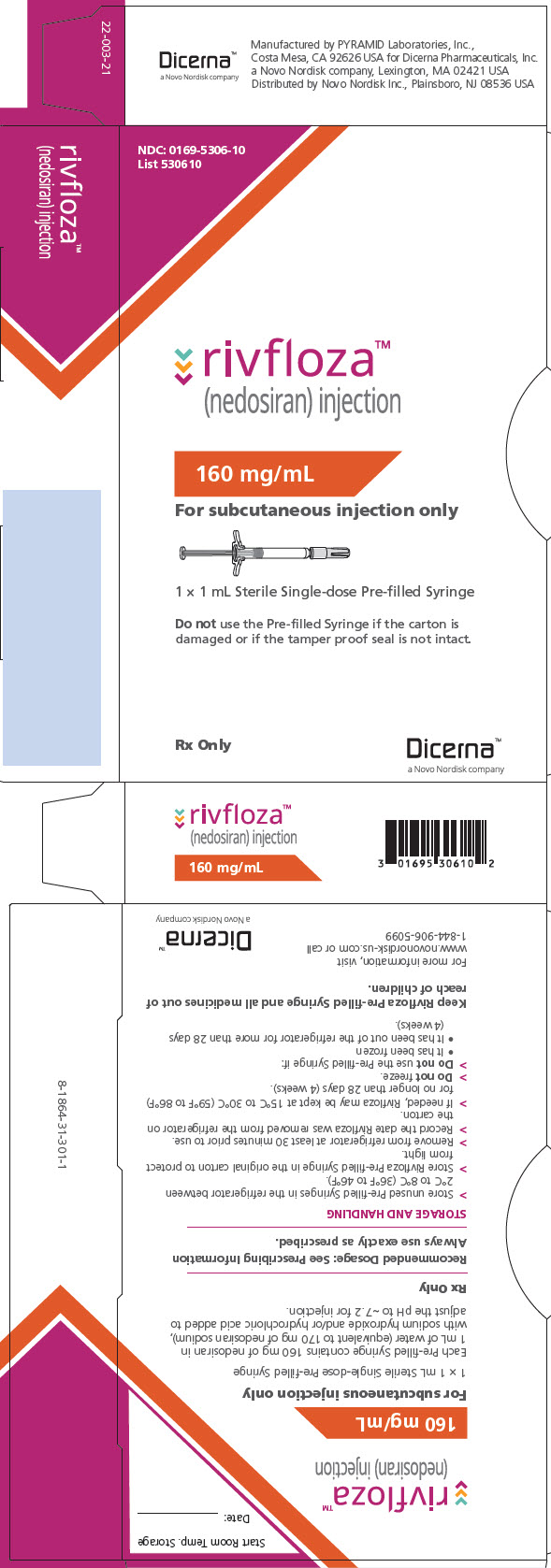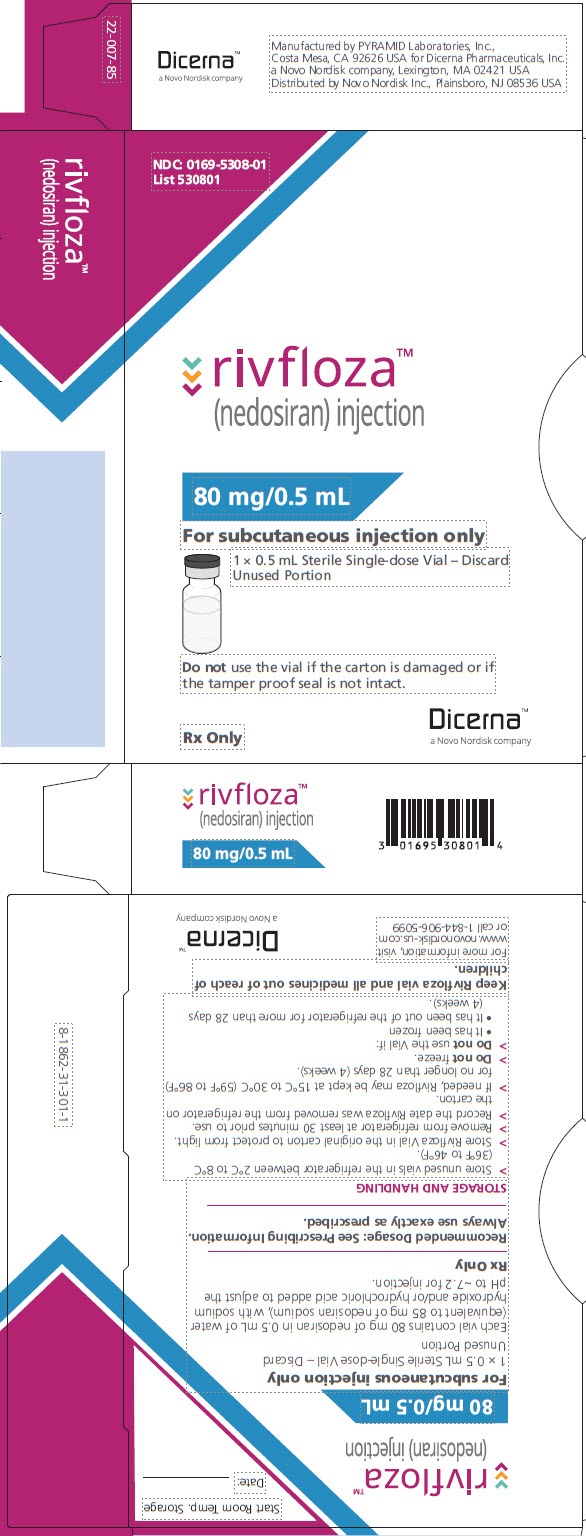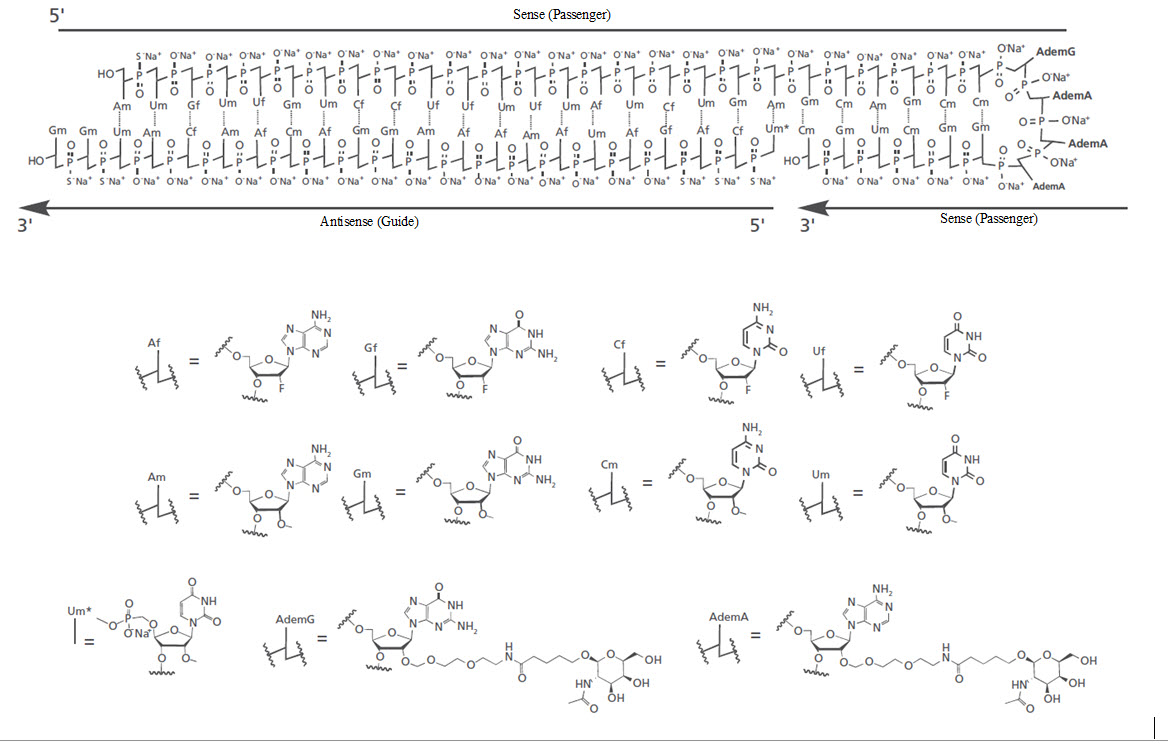 DRUG LABEL: RIVFLOZA
NDC: 0169-5306 | Form: INJECTION, SOLUTION
Manufacturer: Novo Nordisk
Category: prescription | Type: HUMAN PRESCRIPTION DRUG LABEL
Date: 20250303

ACTIVE INGREDIENTS: NEDOSIRAN SODIUM 160 mg/1 mL
INACTIVE INGREDIENTS: WATER

HIGHLIGHTS OF PRESCRIBING INFORMATION

These highlights do not include all the information needed to use RIVFLOZA safely and effectively. See full prescribing information for RIVFLOZA.
RIVFLOZA® (nedosiran) injection, for subcutaneous use
Initial U.S. Approval: 2023

1 INDICATIONS AND USAGE

RIVFLOZA is an LDHA-directed small interfering RNA indicated to lower urinary oxalate levels in children 2 years of age and older and adults with primary hyperoxaluria type 1 (PH1) and relatively preserved kidney function, e.g., eGFR ≥30 mL/min/1.73 m^2. (‎1)

2 DOSAGE AND ADMINISTRATION

The recommended dosage is shown below and is administered subcutaneously once monthly. (‎2.1)

 | Body weight
 | Less than 39 kg | 39 kg to less than 50 kg | 50 kg and above
Age 2 to less than 12 years | 3.3 mg/kg | 128 mg | 160 mg
Age 12 years and older | 128 mg |  | 160 mg

See full Prescribing Information for important administration instructions. (‎2.2)

3 DOSAGE FORMS AND STRENGTHS

RIVFLOZA Injection 160 mg/mL is a clear, colorless-to-yellow solution available as follows:

- 80 mg/0.5 mL single-dose vial
- 128 mg/0.8 mL single-dose Pre-filled Syringe
- 160 mg/ mL single-dose Pre-filled Syringe (‎3)

4 CONTRAINDICATIONS

None. (4)

6 ADVERSE REACTIONS

Most common adverse reactions (reported in ≥20% of patients) are injection site reactions. (‎6.1)

To report SUSPECTED ADVERSE REACTIONS, contact Novo Nordisk Inc. at 1-844-906-5099 or FDA at 1-800-FDA-1088 or www.fda.gov/medwatch.

FULL PRESCRIBING INFORMATION

1 INDICATIONS AND USAGE

RIVFLOZA is indicated to lower urinary oxalate levels in children 2 years of age and older and adults with primary hyperoxaluria type 1 (PH1) and relatively preserved kidney function, e.g., eGFR ≥30 mL/min/1.73 m^2 [see Clinical Pharmacology (‎12.3)], Clinical Studies (‎14.1)].

2 DOSAGE AND ADMINISTRATION

2.1 Recommended Dosage

RIVFLOZA is administered subcutaneously once monthly at the recommended doses shown in Table 1.

Dosing is based on actual body weight.

Table 1: RIVFLOZA Dose Regimen in Adults and Pediatric Patients (2 years of age and older)

 | Body weight
 | Less than 39 kg | 39 kg to less than 50 kg | 50 kg and above
Age 2 to less than 12 years | 3.3 mg/kg | 128 mg | 160 mg
Age 12 years and older | 128 mg |  | 160 mg

Missed Dose

If a planned dose is missed, administer RIVFLOZA as soon as possible. If the planned dose is missed by more than 7 days, administer RIVFLOZA as soon as possible and resume monthly dosing from the most recently administered dose.

2.2 Administration Instructions

Pre-filled syringe: A healthcare provider, caregiver, or patient 12 years of age and older may inject RIVFLOZA using the pre-filled syringe. In pediatric patients 2 to less than 12 years of age who weigh ≥39 kg, a healthcare provider or caregiver may inject RIVFLOZA using the pre-filled syringe.

Vials: RIVFLOZA vials are intended for use under the guidance and supervision of a healthcare provider. Adult patients or caregivers may administer RIVFLOZA after proper training in preparing RIVFLOZA vials for administration, if a healthcare provider determines that it is appropriate, and with medical follow-up as necessary.

Administer RIVFLOZA by subcutaneous injection to the abdomen (at least 2 inches from the navel) or the upper thigh. Do not inject into a vein or into scarred or bruised skin.

Inspect visually for particulate matter and discoloration prior to injection. RIVFLOZA should be colorless-to-yellow and particle free. If the solution is cloudy or contains particulate matter, do not use.

Instructions for delivering the dosage are provided in the Instructions for Use leaflets enclosed with the RIVFLOZA Pre-filled Syringe and single-dose vial.

Discard the unused portion of the drug.

3 DOSAGE FORMS AND STRENGTHS

RIVFLOZA Injection 160 mg/mL (present as 170 mg nedosiran sodium) is a clear, colorless-to-yellow solution available as follows:

- 80 mg/0.5 mL single-dose vial
- 128 mg/0.8 mL single-dose Pre-filled Syringe
- 160 mg/ mL single-dose Pre-filled Syringe

4 CONTRAINDICATIONS

None.

6 ADVERSE REACTIONS

6.1 Clinical Trials Experience

Because clinical trials are conducted under widely varying conditions, adverse reaction rates observed in the clinical trials of a drug cannot be directly compared to rates in the clinical trials of another drug and may not reflect the rates observed in practice.

The safety of RIVFLOZA has been evaluated in one placebo-controlled clinical trial (PHYOX2) and one open-label extension study (PHYOX3). Across these studies, 29 adults and 12 children with PH1 have been treated with RIVFLOZA. Patients with PH1 in these studies ranged in age from 9 to 46 years at first dose. The median duration of exposure was approximately 15 months (range 1-29 months). Overall, 38 patients with PH1 were treated for at least 6 months, 24 patients for at least 12 months, and 16 patients for at least 18 months.

In the randomized, placebo-controlled, double-blind PHYOX2 trial in pediatric and adult patients 9 to 46 years of age, 18 patients with PH1 received RIVFLOZA and 11 patients received placebo. Of the 18 patients treated with RIVFLOZA, 17 patients received ≥5 months of active treatment. The most common adverse reactions were injection site reactions, which were reported in 7 patients with PH1 (39%) on RIVFLOZA as compared to no patients on placebo. Injection site reactions included erythema, pain, bruising, and rash and were generally mild and did not lead to discontinuation of treatment.

In the single-arm extension study (PHYOX3) that included 40 patients with PH1, additional injection site reactions included atrophy in 1 patient (3%).

The safety of RIVFLOZA has additionally been evaluated in one single-arm clinical study (PHYOX8) in 15 pediatric patients 2 to less than 12 years of age with PH1 and an eGFR >30 mL/min/1.73 m^2. Injection site reactions were reported in 2 patients (13%). Overall, the RIVFLOZA safety profile was similar to that seen in PHYOX2.

8 USE IN SPECIFIC POPULATIONS

8.1 Pregnancy

Risk Summary

Available data from reports of pregnancy in clinical trials with RIVFLOZA are insufficient to evaluate for a drug-associated risk of major birth defects, miscarriage or other adverse maternal or fetal outcomes.

In animal reproduction studies, no adverse developmental effects were observed when nedosiran was administered to pregnant mice at doses up to approximately 58 times the maximum recommended human dose (MRHD) of 160 mg nedosiran (equivalent to 170 mg nedosiran sodium) per dose, based on body surface area (BSA) or upon administration of a mouse-specific (pharmacologically active) analog. Subcutaneous administration of nedosiran to pregnant rabbits during the period of organogenesis at doses approximating the MRHD resulted in increased fetal loss in the presence of maternal toxicity. Adverse developmental outcomes (fetal cardiovascular and skeletal malformations) were observed at a dose approximately 2 times the MRHD (see Data). Nedosiran is not pharmacologically active in rabbits or mice. The cause for the embryo-fetal toxicities observed in rabbits remains unclear.

The estimated background risk of major birth defects and miscarriage in the indicated population is unknown. All pregnancies have a background risk of birth defect, loss, or other adverse outcomes. In the U.S. general population, the estimated background risk of major birth defects and miscarriage in clinically recognized pregnancies is 2% to 4% and 15% to 20%, respectively.

Data

Animal Data

In mice, subcutaneous administration of nedosiran at doses up to 2000 mg/kg/dose (approximately 58 times the MRHD based on BSA) or a mouse-specific (pharmacologically active) analog (10 mg/kg/dose) during organogenesis (dosing on gestation days 6, 8, 10, 12, and 14 for nedosiran; gestation days 3 and 10 for the analog) did not have adverse effects on embryo-fetal development.

Subcutaneous administration of nedosiran (0, 2, 6 or 20 mg/kg/dose) to pregnant rabbits during organogenesis (dosing on gestation days 7, 9, 11, 13, 15, 17, and 19) resulted in maternal toxicity on the basis of body weight loss of up to 6.5% following the first dose in the 6 and 20 mg/kg/dose groups. Higher post-implantation loss and lower numbers of live fetuses occurred at ≥6 mg/kg/dose (exposures equivalent to the MRHD based on BSA), and fetal cardiovascular and skeletal malformations occurred at the 20 mg/kg/dose (2 times the MRHD based on BSA). At the 2 mg/kg/dose, which is below the MRHD, no adverse findings were seen.

In a pre- and postnatal study in mice, subcutaneous administration of nedosiran (0, 250, 500, or 1000 mg/kg/dose) or a mouse-specific (pharmacologically active) analog (10 mg/kg/dose) from implantation (dosing on gestational days 6, 8, 10, 12, 14, 16) to weaning (dosing on lactation days 1, 8, 15, 20) did not have adverse effects on the growth, viability, development and reproductive performance of the offspring.

8.2 Lactation

Risk Summary

There are no data on the presence of RIVFLOZA in human or animal milk, the effects on the breastfed child, or the effects on milk production. The developmental and health benefits of breastfeeding should be considered along with the mother’s clinical need for RIVFLOZA and any potential adverse effects on the breastfed infant from RIVFLOZA or from the underlying maternal condition.

8.4 Pediatric Use

The safety and effectiveness of RIVFLOZA have been established in pediatric patients aged 2 years and older. Use of RIVFLOZA in these age groups is supported by evidence from an adequate and well-controlled trial in adult and pediatric patients 9 years of age and older (PHYOX2), and a single-arm study in pediatric patients 2 to less than 12 years of age (PHYOX8) [see Clinical Studies (‎14)].

The safety and effectiveness of RIVFLOZA in patients younger than 2 years of age have not been established.

8.5 Geriatric Use

Clinical studies of RIVFLOZA did not include patients aged 65 and over to determine whether they respond differently from younger patients. No dose adjustment is recommended in patients ≥65 years old [see Clinical Pharmacology (‎12.3)].

8.6 Hepatic Impairment

No dose adjustment of RIVFLOZA is recommended for patients with mild hepatic impairment (total bilirubin ≤ upper limit of normal [ULN] and aspartate aminotransferase [AST] > ULN or total bilirubin >1 to 1.5 times ULN and any AST).

RIVFLOZA has not been studied in patients with moderate or severe hepatic impairment (total bilirubin >1.5 ULN with any AST) [see Clinical Pharmacology (‎12.3)].

8.7 Renal Impairment

No dose adjustment is recommended in patients with an estimated glomerular filtration rate (eGFR) of ≥30 mL/min/1.73 m^2 [see Clinical Pharmacology (‎12.3)].

RIVFLOZA has not been studied in PH1 patients with severe renal impairment (eGFR <30 mL/min/1.73 m^2).

11 DESCRIPTION

RIVFLOZA injection contains nedosiran, a double-stranded small interfering RNA (siRNA) with four covalently attached N-acetyl-D-galactosamine (GalNAc) residues. Nedosiran targets lactate dehydrogenase A (LDHA) in hepatocytes via GalNAc-mediated delivery.

The structural formula of the nedosiran sodium drug substance is presented below:

The molecular formula of nedosiran sodium is C662H808F19N231O413P57S6Na57 with a molecular weight of 22,238 Da. Nedosiran sodium is freely soluble in water.

RIVFLOZA Pre-filled Syringe is supplied as a clear, sterile, preservative-free, colorless‑to‑yellow solution for subcutaneous injection containing either the equivalent of 160 mg (present as 170 mg nedosiran sodium salt) nedosiran in 1 mL or the equivalent of 128 mg (present as 136 mg nedosiran sodium salt) nedosiran in 0.8 mL of water for injection and sodium hydroxide and/or hydrochloric acid to adjust the pH to ~7.2.

RIVFLOZA vial is supplied as a clear, sterile, preservative-free, colorless-to-yellow solution for subcutaneous injection containing the equivalent of 80 mg (present as 85 mg nedosiran sodium salt) nedosiran in 0.5 mL of water for injection and sodium hydroxide and/or hydrochloric acid to adjust the pH to ~7.2.

12 CLINICAL PHARMACOLOGY

12.1 Mechanism of Action

Nedosiran is a double-stranded siRNA, conjugated to GalNAc aminosugar residues. After subcutaneous administration, the GalNAc-conjugated sugars bind to asialoglycoprotein receptors (ASGPR) to deliver nedosiran to hepatocytes.

Nedosiran reduces levels of hepatic lactate dehydrogenase (LDH) via the degradation of LDHA messenger ribonucleic acid (mRNA) in hepatocytes through RNA interference. The reduction of hepatic LDH by nedosiran reduces the production of oxalate by the liver, thereby reducing subsequent oxalate burden.

12.2 Pharmacodynamics

The pharmacodynamic effects of RIVFLOZA were evaluated after single-dose and monthly-dose administration in patients with PH1. Dose-dependent reductions in urinary oxalate were observed in the single-dose range of 1.5 mg/kg to 6.0 mg/kg. With the recommended monthly dose regimen of RIVFLOZA, onset of effect was observed at the first measurement (30 days after the first dose) and the effect persisted with continued monthly dosing [see Clinical Studies (‎14.1)].

Cardiac Electrophysiology

At the recommended dose, RIVFLOZA does not lead to clinically relevant QT interval prolongation.

12.3 Pharmacokinetics

The pharmacokinetic (PK) properties of RIVFLOZA were evaluated following administration of single and multiple dosages in patients with PH1 or PH2 as summarized in Table 2.

Table 2: Pharmacokinetic Parameters of Nedosiran

 |  | Nedosiran
General Information
Steady State Exposure | Cmax [Mean (%CV)] | 844 (44) ng/mL
Steady State Exposure | AUC0-last [Mean (%CV)] | 13600 (36) ng*h/mL
Dose Proportionality |  | Nedosiran exhibited a dose-proportional increase in plasma exposure following single subcutaneous doses from 1.5 to 6.0 mg/kg.; Nedosiran exhibited time-independent pharmacokinetics with multiple doses of 160 mg once monthly (body weight ≥50 kg), 128 mg once monthly (body weight <50 kg), or 3.3 mg/kg once monthly in the age range of 6 to 11 years.
Accumulation |  | No accumulation of nedosiran was observed in plasma following repeated monthly dosing.
Absorption
Tmax [Median (Range)] |  | 6 (2 to 12) hours
Distributiona
Estimated Vz/F |  | 126 L
Protein Binding |  | 85.6%
Elimination
Half-Life (Mean (%CV)]) |  | 15 (68) hours
Estimated CL/F |  | 5.7 L/hr
Metabolism
Primary Pathway |  | Nedosiran is metabolized by endo- and exonucleases to shorter oligonucleotides.
Excretion
Primary Pathway |  | Approximately 27% of the administered nedosiran dose is excreted unchanged into the urine within 24 hours of dosing.
a Nedosiran distributes primarily to the liver after subcutaneous administration.
Cmax = maximum plasma concentration; AUC0-last = area under the plasma concentration-time curve from time of administration (0) to the last measurable time point (last); Tmax = time to maximum concentration; Vz/F = apparent volume of distribution; CV = coefficient of variation; CL/F = apparent clearance.

Specific Populations

No clinically significant differences in the pharmacokinetics or pharmacodynamics of nedosiran were observed based on age (2 to 73 years old), sex, race/ethnicity, mild-to-moderate renal impairment (eGFR 30 to 89 mL/min/1.73 m^2) [see Use in Specific Populations (‎8.7)] or mild hepatic impairment as assessed using the National Cancer Institute Organ Dysfunction Working Group criteria (total bilirubin ≤ ULN and AST > ULN; or total bilirubin >1 to 1.5 × ULN and any AST) [see Use in Specific Populations (‎8.6)].

Pediatrics:

At the recommended clinical dose, PK exposure of nedosiran is similar in adult and pediatric patients 2 years of age and older.

Drug Interaction Studies

Concomitant use of pyridoxine (vitamin B6) did not have a significant impact on the PK of nedosiran.

In vitro studies demonstrated that nedosiran was not an inhibitor or inducer of cytochrome P450 (CYP) enzymes and was neither a substrate nor an inhibitor of efflux and uptake transporters.

12.6 Immunogenicity

As with all oligonucleotides, including RIVFLOZA, there is a potential for immunogenicity. The detection of antibody formation is highly dependent on the sensitivity and specificity of the assay. Additionally, the observed incidence of antibody positivity in an assay may be influenced by several factors, including assay methodology, sample handling, timing of sample collection, concomitant medications, and underlying disease. For these reasons, comparison of the incidence of antibodies in the studies described below with the incidence of antibodies in other studies or to other products may be misleading.

Across all clinical studies in the nedosiran development program, including patients with PH1 dosed with RIVFLOZA, RIVFLOZA did not induce or boost anti-drug antibodies (ADA). Among 79 patients tested with the ADA assay, none developed treatment-emergent ADA.

13 NONCLINICAL TOXICOLOGY

13.1 Carcinogenesis, Mutagenesis, Impairment of Fertility

Carcinogenicity

Long-term studies to assess carcinogenic risk of nedosiran have not been conducted.

Genotoxicity

Nedosiran was not genotoxic in the in vitro bacterial mutagenicity, in vitro micronucleus assays (human peripheral blood lymphocytes) and in vivo bone marrow micronucleus assay in mice.

Fertility

Weekly subcutaneous administration of nedosiran at doses of 500, 1000, or 2000 mg/kg or of a mouse-specific (pharmacologically active) analog at a dose of 10 mg/kg to male mice for 4 weeks prior to and throughout mating, and to female mice for 2 weeks prior to and throughout mating and to gestation day 7 did not affect male or female fertility or early embryonic development.

14 CLINICAL STUDIES

14.1 PHYOX2

PHYOX2 was a randomized, double-blind trial comparing RIVFLOZA and placebo in patients aged 6 years or older with PH1 or PH2 and an eGFR ≥ 30 mL/min/1.73 m^2 (NCT03847909). Too few PH2 patients were enrolled to evaluate efficacy in the PH2 population. Therefore, RIVFLOZA is only indicated for patients with PH1 [see Indications and Usage (1)]. Unless otherwise noted, data are presented for the complete study population (PH1 and PH2).

Patients received monthly doses of RIVFLOZA (N=23) or placebo (N=12). The RIVFLOZA dose for patients at least 12 years of age weighing at least 50 kg was 160 mg, for patients at least 12 years of age weighing less than 50 kg was 128 mg, and for children 6 to 11 years of age was 3.3 mg/kg (to a maximum of 128 mg).

The median age was 20 years (range 9 - 46 years), 51% were female, 71% were White, 17% were Asian, 83% had PH1, and 17% had PH2. At baseline, mean 24-hour urinary oxalate excretion, normalized by 1.73 m^2 BSA in patients less than 18 years of age, was 1547 µmol/24‑hour. Mean plasma oxalate was 8.2 µmol/L, 43% of patients had an eGFR ≥ 90 mL/min/1.73 m^2, 34% had an eGFR 60 to < 90 mL/min/1.73 m^2, 23% had an eGFR 30 to < 60 mL/min/1.73 m^2, and 60% were taking pyridoxine.

The primary efficacy endpoint was the area under the curve, from Days 90 to 180, of the percent change from baseline in 24-hour urinary oxalate excretion (AUC24-hour Uox). The least-squares (LS) mean AUC24‑hour Uox was -3486 (95% CI: -5025, -1947) in the RIVFLOZA group compared to 1490 (95% CI: 781, 3761) in the placebo group, for a between group difference of 4976 (95% CI: 2803, 7149; p<0.0001).

The LS mean percent change from baseline in 24-hour urinary oxalate excretion (corrected for BSA in patients < 18 years of age) averaged over Days 90, 120, 150 and 180, was -37% (95% CI: -53%, -21%) in the RIVFLOZA group and 12% (95% CI: ‑12%, 36%) in the placebo group, for a between group difference of 49% (95% CI: 26%, 72%) [Figure 1]. Among patients with PH1, the between group difference was 56% (95% CI: 33%, 80%).

Figure 1. Mean (95% CI) Percent Change from Baseline in 24-hour Urinary Oxalate in RIVFLOZA and Placebo-Treated Patients in PHYOX2

After 6 months of treatment in PHYOX2, patients could enroll in an ongoing single-arm extension study, PHYOX3 (NCT04042402), in which all patients were treated with RIVFLOZA. The reduction in urinary oxalate was maintained in the 13 patients with PH1 who received an additional 6 months of treatment in PHYOX3.

14.2 PHYOX8

PHYOX8 (NCT05001269) was a single-arm open-label multicenter study that included patients 2 years of age to less than 12 years of age with PH1 and an eGFR >30 mL/min/1.73 m^2.

The median age of patients at first dose was 5 years (range 2 to 10 years), 33% were female, and 80% were White. A total of 15 patients with PH1 completed treatment; 8 patients were 2 to less than 6 years of age, 5 patients were 6 to less than 9 years of age and 2 patients were 9 to 11 years of age. The mean spot urinary oxalate:creatinine ratio at baseline was 0.36 mmol/mmol.

The primary endpoint was the percent change from baseline in spot urinary oxalate:creatinine ratio at Month 6. Patients treated with RIVFLOZA had a 64% (95% CI: 44, 84) reduction in spot urinary oxalate:creatinine ratio from baseline at Month 6 (Figure 2). The corresponding absolute reduction in spot urinary oxalate:creatinine ratio at Month 6 was 0.25 mmol/mmol (95% CI: 0.21, 0.29).

Figure 2. PHYOX8: Mean (95% CI) Percent Change in Spot Urinary Oxalate: Creatinine Ratio from Baseline by Month

After 6 months of treatment in PHYOX8, patients could enroll in an ongoing single arm extension study, PHYOX3. The reduction in urinary oxalate:creatinine ratio was maintained in the 8 patients who received an additional 6 months of treatment in PHYOX3.

16 HOW SUPPLIED/STORAGE AND HANDLING

16.1 How Supplied

RIVFLOZA is a clear, sterile, preservative-free, colorless-to-yellow solution available in single-dose pre-filled syringes and single-dose vials in cartons containing one unit each.

Table 3: RIVFLOZA Presentations

RIVFLOZA Presentation | Total Volume | Total amount available in presentation | Concentration | NDC number
Single-dose vial | 0.5 mL | 80 mg | 160 mg/mL | NDC 0169-5308-01
Single-dose; Pre-filled Syringe | 0.8 mL | 128 mg | 160 mg/mL | NDC 0169-5307-08
Single-dose; Pre-filled Syringe | 1 mL | 160 mg | 160 mg/mL | NDC 0169-5306-10

16.2 Storage and Handling

Store refrigerated at 2°C to 8°C (36°F to 46°F). RIVFLOZA can be stored, if needed, at 15°C to 30°C (59°F to 86°F) for a maximum of 28 days (4 weeks). Do not freeze. Store in original carton, away from direct heat and light.

Table 4: Storage Conditions for RIVFLOZA

 | Refrigerated; 2°C to 8°C (36°F to 46°F) | Room Temperature at 15°C to 30°C; (59°F to 86°F)
RIVFLOZA | Until expiration date | Maximum 28 days (4 weeks)

17 PATIENT COUNSELING INFORMATION

Advise the patient to read the FDA-approved patient labeling (Patient Information and Instructions for Use).
2. Instruct patients/caregivers on the appropriate dose of RIVFLOZA to use, the timing of the dose, how and where to inject subcutaneously, and what to do if a dose is missed.

For more information contact:
Dicerna Pharmaceuticals, Inc.
A Novo Nordisk company

Novo Nordisk Inc.
800 Scudders Mill Road
Plainsboro, NJ 08536
1-844-906-5099

Manufactured by
Pyramid Laboratories
3598 Cadillac Ave
Costa Mesa, CA 92626

Patient Package Insert

PATIENT INFORMATION

RIVFLOZA® (Riv-flo-za)

(nedosiran)

injection, for subcutaneous use

What is RIVFLOZA?

RIVFLOZA is a prescription medicine used to lower urinary oxalate levels in children 2 years of age and older and adults with primary hyperoxaluria type 1 (PH1) and relatively preserved kidney function.

It is not known if RIVFLOZA is safe and effective in children younger than 2 years of age.

Before using RIVFLOZA, tell your healthcare provider about all of your medical conditions, including if you:

- are pregnant or plan to become pregnant. It is not known if RIVFLOZA will harm your unborn baby.
- are breastfeeding or plan to breastfeed. It is not known if RIVFLOZA passes into your breast milk. Talk to your healthcare provider about the best way to feed your baby during treatment with RIVFLOZA.

Tell your healthcare provider about all the medicines you take, including prescription and over-the-counter medicines, vitamins, and herbal supplements.

How should I use RIVFLOZA?

- Read the detailed Instructions for Use that comes with RIVFLOZA about the right way to prepare and inject RIVFLOZA.
- Use RIVFLOZA exactly as your healthcare provider tells you to.
- Inject RIVFLOZA under your skin (subcutaneous injection).
- Use RIVFLOZA 1 time each month.
- Your healthcare provider will prescribe the dose of RIVFLOZA that is right for you or your child based on your or your child’s body weight.
- RIVFLOZA comes as a single-dose Pre-filled Syringe and as a single-dose vial.
- Your healthcare provider will show you or your caregiver how to prepare and inject RIVFLOZA. Do not try to inject RIVFLOZA until you or your caregiver have been shown the right way by your healthcare provider.
- In children 2 years of age to less than 12 years of age weighing 86 pounds (39 kilograms) or more, it is recommended that RIVFLOZA Pre-filled Syringe be given by a healthcare provider or caregiver.
- If you miss a dose of RIVFLOZA, inject the dose as soon as possible. If you miss a dose of RIVFLOZA by more than 7 days, inject the dose as soon as possible and resume monthly dosing from the most recently injected dose. If you have any questions about a missed dose, call your healthcare provider or pharmacist.

What are the possible side effects of RIVFLOZA?

The most common side effects of RIVFLOZA include injection site reactions, such as reddening, pain, bruising, rash, or dimple at the site of injection.

These are not all the possible side effects of RIVFLOZA.

Call your doctor for medical advice about side effects. You may report side effects to FDA at 1-800-FDA-1088.

You may also report side effects to Novo Nordisk at 1-844-906-5099.

How should I store RIVFLOZA?

- Store RIVFLOZA in the refrigerator between 36°F to 46°F (2°C to 8°C).
- If needed, RIVFLOZA can be stored between 59°F to 86°F (15°C to 30°C) for up to 28 days (4 weeks). Record the date RIVFLOZA was removed from the refrigerator on the carton and throw away (dispose of) if not used within 28 days.
- Do not freeze RIVFLOZA.
- Store RIVFLOZA in the original carton.
- Keep RIVFLOZA away from direct heat and light.

Keep RIVFLOZA and all medicines out of the reach of children.

General information about the safe and effective use of RIVFLOZA.

Medicines are sometimes prescribed for purposes other than those listed in a Patient Information leaflet. Do not use RIVFLOZA for a condition for which it was not prescribed. Do not give RIVFLOZA to other people, even if they have the same symptoms that you have. It may harm them. You can ask your pharmacist or healthcare provider for information about RIVFLOZA that is written for health professionals.

What are the ingredients in RIVFLOZA?

Active ingredient: nedosiran

Inactive ingredients: water for injection and sodium hydroxide and/or hydrochloric acid.

For more information contact: Dicerna Pharmaceuticals, Inc., A Novo Nordisk company

Novo Nordisk Inc., 800 Scudders Mill Road, Plainsboro, NJ 08536

1-844-906-5099

Manufactured by: Pyramid Laboratories, 3598 Cadillac Ave, Costa Mesa, CA 92626

For more information, go to https://www.rivfloza.com/ or call 1-844-906-5099.

This Patient Information has been approved by the U.S. Food and Drug Administration. Revised: 03/2025

Instructions for Use – Pre-filled Syringe

INSTRUCTIONS FOR USE

RIVFLOZA® (Riv-flo-za)
(nedosiran)

injection, for subcutaneous use

Single-dose Pre-filled Syringe

This Instructions for Use contains information on how to inject RIVFLOZA.

Read the Instructions for Use before using RIVFLOZA Pre-filled Syringe and each time you get a refill. There may be new information. Ask your or your child’s healthcare provider if you have any questions.

RIVFLOZA Pre-filled Syringe Parts

RIVFLOZA Pre-filled Syringe is available in 2 dose strengths. You should check the label on the carton that comes with the RIVFLOZA Pre-filled Syringe to make sure you have the right Pre-filled Syringe for the prescribed dose.

For adults and children 12 years of age and older weighing less than 110 pounds (50 kilograms)

and

For children 2 years of age to less than 12 years of age weighing between 86 pounds (39 kilograms) and less than 110 pounds (50 kilograms):

RIVFLOZA®

(nedosiran) injection

For subcutaneous injection only

For adults and children 2 years of age and older weighing 110 pounds (50 kilograms) or more:

RIVFLOZA®

(nedosiran) injection

For subcutaneous injection only

Important information you need to know before injecting RIVFLOZA.

- Your or your child’s healthcare provider will show you how to prepare and inject RIVFLOZA before you use the Pre-filled Syringe for the first time.
- Use RIVFLOZA Pre-filled Syringe exactly as your or your child’s healthcare provider tells you to.
- In children 2 years of age to less than 12 years of age it is recommended that RIVFLOZA Pre-filled Syringe be given by a healthcare provider or caregiver.
- Your or your child’s healthcare provider will tell you when and how to inject RIVFLOZA.
- RIVFLOZA Pre-filled Syringe is a single-dose Pre-filled Syringe for one-time (single) use only. Do not reuse the Pre-filled Syringe.
- Do not use the Pre-filled Syringe if the carton is damaged or if the tamper-proof seal is not intact.
- Do not use if the expiration date on the carton has passed.
- RIVFLOZA Pre-filled Syringe is for injection under the skin (subcutaneous injection) only. Do not inject RIVFLOZA into a vein.

Supplies needed to give the injection:

- 1 RIVFLOZA Pre-filled Syringe
The following supplies are not included in the carton:
- Alcohol wipe
- Cotton balls or gauze
- Puncture resistant sharps disposal container. See Step 12 “Throw away (dispose of) the used RIVFLOZA Pre-filled Syringe” at the end of this Instructions for Use.

How should I store RIVFLOZA Pre-filled Syringe?

- Store unused RIVFLOZA Pre-filled Syringes in the refrigerator between 36°F to 46°F (2°C to 8°C).
- If needed, RIVFLOZA Pre-filled Syringes can be stored between 59°F to 86°F (15°C to 30°C) for no longer than 28 days (4 weeks). Record the date RIVFLOZA was removed from the refrigerator on the carton and throw away (dispose of) if not used within 28 days.
- Store RIVFLOZA Pre-filled Syringes in the original carton.
- Keep RIVFLOZA Pre-filled Syringes away from direct heat and light.
- Do not freeze.

Keep RIVFLOZA Pre-filled Syringe and all medicines out of the reach of children.

INSTRUCTIONS FOR USE

A. Preparing for the injection

Step 1. Gather the supplies and place the supplies on a clean, flat surface in a well-lit area.

Step 2. Remove the RIVFLOZA Pre-filled Syringe carton from the refrigerator.

- Make sure the carton contains the correct dose.
- Check the expiration date on the carton. Do not use if the expiration date has passed.
- Wait 30 minutes before injecting to allow the medicine in the Pre-filled Syringe to warm to room temperature.

Caution:

- Keep the RIVFLOZA Pre-filled Syringe in the carton and out of direct heat and sunlight.
- Do not warm the Pre-filled Syringe using any heat sources such as hot water or a microwave.

Step 3. Wash your hands with soap and water.

Step 4. Open the carton and remove the RIVFLOZA Pre-filled Syringe.

- Grip the barrel of the Pre-filled Syringe and remove it from the carton.

Step 5. Inspect the RIVFLOZA Pre-filled Syringe.

- Look at the medicine in the Pre-filled Syringe. The medicine should be colorless to yellow and free of particles.
- Do not use the Pre-filled Syringe if the medicine looks cloudy, discolored, or contains particles.
- The Pre-filled Syringe should not look damaged.
  - Do not use the Pre-filled Syringe if it looks damaged.

You may see small air bubbles in the liquid. This is normal.

Step 6. Choose the injection site.

You may inject into skin of:

- the stomach area (abdomen) at least 2 inches from the belly button, or
- the upper thigh.

Caution:

- Do not inject into scarred or bruised skin.

Step 7. Clean the injection site.

- Clean the injection site with an alcohol wipe and let it air dry.
- Do not touch, wipe with other material, fan, or blow on the cleaned injection site.

B. Giving the injection

Step 8. Remove the needle cap and throw it away in the sharps disposal container.

- Hold the Pre-filled Syringe with 1 hand and the needle pointed away from you. Pull the needle cap straight off with your other hand as shown.

Caution:

- If the needle appears to be bent or damaged, do not use the Pre-filled Syringe.
- Do not touch or recap the needle.
- Do not touch the plunger rod until you are ready to inject.

Step 9. Pinch the skin and fully insert the needle.

- Pinch the skin around the clean injection site with 1 hand.
- Grasp the finger grip of the Pre-filled Syringe with your other hand and fully insert the needle into the injection site at a 45-degree angle.

Step 10. Slowly inject all the medicine.

- Gently push the plunger rod all the way down until the Pre-filled Syringe is empty.
- You will see the rubber stopper inside the Pre-filled Syringe move to the bottom of the barrel as the medicine is injected.

Step 11. Remove the RIVFLOZA Pre-filled Syringe from the injection site.

Caution:

- Do not recap the needle.

If there is bleeding, lightly press a cotton ball or gauze over the injection site.

C. After the injection

Step 12. Throw away (dispose of) the used RIVFLOZA Pre-filled Syringe.

- Put the used RIVFLOZA Pre-filled Syringe in an FDA-cleared sharps disposal container right away after use.
- Do not throw away (dispose of) RIVFLOZA Pre-filled Syringes and needle caps in your household trash.
- If you do not have an FDA-cleared sharps disposal container, you may use a household container that is:
- made of a heavy-duty plastic,
- can be closed with a tight-fitting, puncture-resistant lid, without sharps being able to come out,
- upright and stable during use,
- leak-resistant, and
- properly labeled to warn of hazardous waste inside the container.
- When the sharps disposal container is almost full, you will need to follow your community guidelines for the right way to dispose of your sharps disposal container. There may be state or local laws about how you should throw away used needles and syringes.
- For more information about safe sharps disposal, and for specific information about sharps disposal in the state that you live in, go to the FDA’s website at: http://www.fda.gov/safesharpsdisposal.
- Do not dispose of the used sharps disposal container in your household trash unless your community guidelines permit this.
- Do not recycle the used sharps disposal container.

Flip Page for more Information

Frequently asked questions

What if a dose is missed?

- If a dose of RIVFLOZA is missed, inject the dose as soon as possible.
- If a dose of RIVFLOZA is missed by more than 7 days, inject the dose as soon as possible and resume monthly dosing from the most recently injected dose.

If you have any questions about a missed dose, call your healthcare provider or pharmacist.

What if I damage or break the RIVFLOZA Pre-filled Syringe?

- Do not use a broken or damaged Pre-filled Syringe. Call the pharmacy for a replacement.

Do I inject the full volume of the Pre-filled Syringe?

- Yes, the Pre-filled Syringe is for one-time (single) use and contains 1 complete dose.

“Pull Out” panel (on front of IFU)

INSTRUCTIONS FOR USE

Read Entire Instructions Before Use

Follow Instructions Carefully

Contact Novo Nordisk for any Questions

RIVFLOZA® (Riv-flo-za)

(nedosiran) injection,

for subcutaneous use

Single-dose Pre-filled Syringe

Address Panel

For more information go to https://www.rivfloza.com/ or call 1-844-906-5099.

Dicerna Pharmaceuticals, Inc.

A Novo Nordisk company

Novo Nordisk Inc.

800 Scudders Mill Road

Plainsboro, NJ 08536 USA

1-888-906-5099

Manufactured by:

Pyramid Laboratories

3598 Cadillac Avenue

Costa Mesa, CA 92626 USA

Version: 3

© 2025 Novo Nordisk

This Instructions for Use has been approved by the U.S. Food and Drug Administration.

Revised: 03/2025

Flip Page for Instructions for Use

Instructions for Use - Vial

INSTRUCTIONS FOR USE

RIVFLOZA® (Riv-flo-za)

(nedosiran)

injection, for subcutaneous use

Single-dose vial

This Instructions for Use contains information on how to inject RIVFLOZA using the single-dose vial in:

- children 2 years of age to less than 12 years of age weighing less than 86 pounds (39 kilograms).
- adults and children using the single-dose vial as an alternative to the single-dose Pre-filled syringe.

Read the Instructions for Use before using RIVFLOZA vial and each time you get a refill. There may be new information. Ask your or your child’s healthcare provider if you have any questions.

Important information you need to know before injecting RIVFLOZA.

- Your or your child’s healthcare provider will show you how to prepare and inject RIVFLOZA. Do not try to inject RIVFLOZA until you have been shown the right way by your or your child’s healthcare provider.
- Use RIVFLOZA vials exactly as your or your child’s healthcare provider tells you to.
- Your or your child’s healthcare provider will tell you how much RIVFLOZA to inject and when to inject it.
- Do not use the RIVFLOZA vial if the carton is damaged or if the tamper-proof seal is not intact.
- Do not use the RIVFLOZA vial if the expiration date on the carton has passed.
- Uncap the RIVFLOZA vial only when ready to give an injection. Under the vial cap, you will see a grey rubber stopper. Do not remove it. It is supposed to be there.
- RIVFLOZA vials are for one-time use (single-dose) only. Do not reuse the RIVFLOZA vial. Throw away (discard of) any unused RIVFLOZA.
- RIVFLOZA is for injection under the skin (subcutaneous injection) only. Do not inject RIVFLOZA into a vein.

Supplies needed to give the injection

If the amount of RIVFLOZA needed for your or your child’s prescribed dose is 0.5 mL or less, you will need the following supplies:

- 1 RIVFLOZA vial

The following supplies are not included in the carton:

- One 1 mL syringe with attached 27-gauge 1/2” needle
- Alcohol wipes
- Cotton balls or gauze
- Puncture resistant sharps disposal container. See Step 16 “Throw away (dispose of) the used syringe(s)” at the end of this Instructions for Use.

If the amount of RIVFLOZA needed for your or your child’s prescribed dose is 0.6 mL or more, you will need the following supplies:

- 2 RIVFLOZA vials

The following supplies are not included in the carton:

- Two 1 mL syringes with attached 27-gauge 1/2” needle
- Alcohol wipes
- Cotton balls or gauze
- Puncture resistant sharps disposal container. See Step 16 “Throw away (dispose of) the used syringe(s)” at the end of this Instructions for Use.

How should I store RIVFLOZA vials?

- Store RIVFLOZA vials in the refrigerator between 36°F to 46°F (2°C to 8°C).
- If needed, RIVFLOZA vials may be stored between 59°F to 86°F (15°C to 30°C) for no longer than 28 days (4 weeks). Record the date RIVFLOZA was removed from the refrigerator on the carton and throw away (dispose of) if not used within 28 days.
- Store RIVFLOZA in the original carton.
- Keep RIVFLOZA vials away from direct heat and light.
- Do not freeze.

Keep RIVFLOZA vials and all medicines out of the reach of children.

A. Preparing for the injection

Step 1. Gather the supplies and place the supplies on a clean, flat surface in a well-lit area.

Step 2. Remove the RIVFLOZA vial carton(s) from the refrigerator.

- Check the expiration date on the carton. Do not use if the expiration date on the carton has passed.
- Wait 30 minutes before injecting to allow the medicine in the vial to warm to room temperature.

Caution:

- Keep the RIVFLOZA vial in the carton and out of direct heat and sunlight.
- Do not warm the vial using any heat sources such as hot water or a microwave.

Step 3. Wash your hands with soap and water.

Step 4. Open the carton(s) and remove the RIVFLOZA vial(s).

- Check the vial label to make sure you have the correct medicine for the prescription.

Step 5. Inspect the RIVFLOZA vial(s).

- Look at the medicine in the vial. It should be colorless to yellow and free of particles.
  - Do not use the vial if the medicine looks cloudy, discolored, or contains particles.
- The vial should not look damaged.
  - Do not use the vial if the vial looks damaged.

Step 6. Choose the injection site(s).

- You may inject into the skin of:
  - the stomach area (abdomen) at least 2 inches from the belly button, or
  - the upper thigh.
- If the dose is more than 0.5 mL (2 injections), inject the contents of each syringe in a different location. If both injections are in the abdomen, they should be in different areas of the abdomen.

Caution:

- Do not inject into scarred or bruised skin.
- Do not inject the contents of 2 syringes into the same location.

Step 7. Clean the injection site(s).

- Clean the injection site(s) with an alcohol wipe and let it air dry.
- Do not touch, wipe with other material, fan, or blow on the cleaned injection site(s).

Step 8. Prepare the vial(s).

- Remove the cap from the vial(s) you will need.
- Clean the top of the grey rubber stopper with a new alcohol wipe.

Caution:

- Do not remove the grey rubber stopper from the vial. It is supposed to be there.

B. Giving the injection

Step 9. Remove the syringe with attached needle from the packaging and remove the needle cap. Throw the needle cap away in the sharps disposal container.

- Remove the needle cap by pulling it straight off and away from your body.

Caution:

- Take care when handling the uncapped needle.
- Do not touch the uncapped needle.

Step 10. Withdraw RIVFLOZA into the syringe.

If the dose amount is 0.5 mL or less:

- Insert the needle into the grey rubber stopper on top of the vial.
- Turn the vial and syringe upside down.
- Keep the tip of the needle in the medicine.
- Hold the syringe and vial in 1 hand. With your other hand, slowly pull back on the plunger rod to withdraw the prescribed dose into the syringe.

If the dose amount is 0.6 mL or more:

- You will need to withdraw the dose of RIVFLOZA from 2 vials using 2 separate syringes.
- Follow “If the dose amount is 0.5 mL or less” instructions to withdraw the amount of medicine needed from each vial as instructed by your or your child’s healthcare provider. Then follow Steps 11 to 16 for each syringe to inject RIVFLOZA.

Step 11. Remove any large air bubbles from the syringe.

- If you see large air bubbles in the syringe, tap the side of the syringe to move any air bubbles to the top of the syringe.
- Push the plunger rod up to push the air bubbles back into the vial.
- If the syringe does not contain the correct dose after the large air bubbles are removed, you will need to pull back on the plunger rod again to fill the syringe with the prescribed dose.
- Look at the syringe to make sure you have the correct amount for the dose.

Caution:

- Be sure the syringe is free of large air bubbles before you inject.

Step 12. Turn the vial and syringe back upright and remove the needle from the vial.

Step 13. Pinch the skin and fully insert the needle.

- Pinch the skin around the injection site with 1 hand.
- With your other hand, fully insert the needle into the skin at a 45-degree angle.
- If you are giving 2 injections, inject each syringe in a different location. If both injections are in the abdomen, they should be in different areas of the abdomen.

Step 14. Slowly inject all the medicine.

- Gently push the plunger rod all the way down until the syringe is empty.
- You will see the rubber stopper inside the syringe move to the bottom of the barrel as the medicine is injected.

Step 15. Remove the needle from the injection site.

Caution:

- Do not recap the needle.
- Do not save or keep used syringes.

Throw away (dispose of) the used vial(s) in household trash.

If there is bleeding, lightly press a cotton ball or gauze over the injection site.

C. After the injection

Step 16. Throw away (dispose of) the used syringe(s).

- Put the used syringe(s) with the needle still attached in an FDA-cleared sharps container right away after use.
- Do not throw away (dispose of) needles and syringes in your household trash.
- If you do not have an FDA-cleared sharps disposal container, you may use a household container that is:
- made of a heavy-duty plastic,
- can be closed with a tight-fitting, puncture-resistant lid, without sharps being able to come out,
- upright and stable during use,
- leak-resistant, and
- properly labeled to warn of hazardous waste inside the container.
- When the sharps disposal container is almost full, you will need to follow your community guidelines for the right way to dispose of your sharps disposal container. There may be state or local laws about how you should throw away used needles and syringes.
- For more information about safe sharps disposal, and for specific information about sharps disposal in the state that you live in, go to the FDA’s website at: http://www.fda.gov/safesharpsdisposal
- Do not dispose of the used sharps disposal container in your household trash unless your community guidelines permit this.
- Do not recycle the used sharps disposal container.

Flip Page for More Information

Frequently asked questions

What if a dose is missed?

- If a dose of RIVFLOZA is missed, inject the dose as soon as possible.
- If a dose of RIVFLOZA is missed by more than 7 days, inject the RIVFLOZA dose as soon as possible and resume monthly dosing from the most recently injected dose.

If you have any questions about a missed dose, call your healthcare provider or pharmacist.

What if I damage or break the RIVFLOZA vial?

- Do not use a broken or damaged vial. Call the pharmacy for a replacement.

Do I inject the full volume of the vial?

- The amount of RIVFLOZA you will inject depends on the prescribed dose. You may need more than one vial, one vial, or less than one vial for the prescribed dose.

What if I need 2 vials for injection?

- Use 2 separate syringes and withdraw the amount from each vial as directed by your or your child’s healthcare provider. Give 2 separate injections in a different location. If both injections are in the abdomen, they should be in different areas of the abdomen.

“Pull Out” panel (on front of IFU)

INSTRUCTIONS FOR USE

Read Entire Instructions Before Use

Follow Instructions Carefully

Contact Novo Nordisk for any Questions

RIVFLOZA® (Riv-flo-za)

(nedosiran)

injection, for subcutaneous use

Single-dose vial

Address Panel

For more information go to https://www.rivfloza.com/ or call 1-844-906-5099.

Dicerna Pharmaceuticals, Inc.

A Novo Nordisk company

Novo Nordisk Inc.

800 Scudders Mill Road

Plainsboro, NJ 08536 USA

1-888-906-5099

Manufactured by:

Pyramid Laboratories

3598 Cadillac Avenue

Costa Mesa, CA 92626 USA

Version: 3

© 2025 Novo Nordisk

This Instructions for Use has been approved by the U.S. Food and Drug Administration.

Revised: 03/2025

Flip Page for Instructions for Use

PACKAGE/LABEL PRINCIPAL DISPLAY PANEL – Pre-filled Syringe 128 mg/0.8 mL

NDC: 0169-5307-08

List 530708

rivfloza™

(nedosiran) injection

128 mg/0.8 mL

For subcutaneous injection only

1 x 0.8 mL Sterile Single-dose Pre-filled Syringe

Do not use the Pre-filled Syringe if the carton is damaged or if the tamper proof seal is not intact.

Rx Only

Dicerna™

a Novo Nordisk company

PACKAGE/LABEL PRINCIPAL DISPLAY PANEL – Pre-filled Syringe 160 mg/mL

NDC: 0169-5306-10

List 530610

rivfloza™

(nedosiran) injection

160 mg/mL

For subcutaneous injection only

1 x 1 mL Sterile Single-dose Pre-filled Syringe

Do not use the Pre-filled Syringe if the carton is damaged or if the tamper proof seal is not intact.

Rx Only

Dicerna™

a Novo Nordisk company

PACKAGE/LABEL PRINCIPAL DISPLAY PANEL – Vial 80 mg/0.5 mL

NDC: 0169-5308-01

List 530801

rivfloza™

(nedosiran) injection

80 mg/0.5 mL

For subcutaneous injection only

1 x 0.5 mL Sterile Single-dose Vial – Discard Unused Portion

Do not use the vial if the carton is damaged or if the tamper proof seal is not intact.

Rx Only

Dicerna™

a Novo Nordisk company